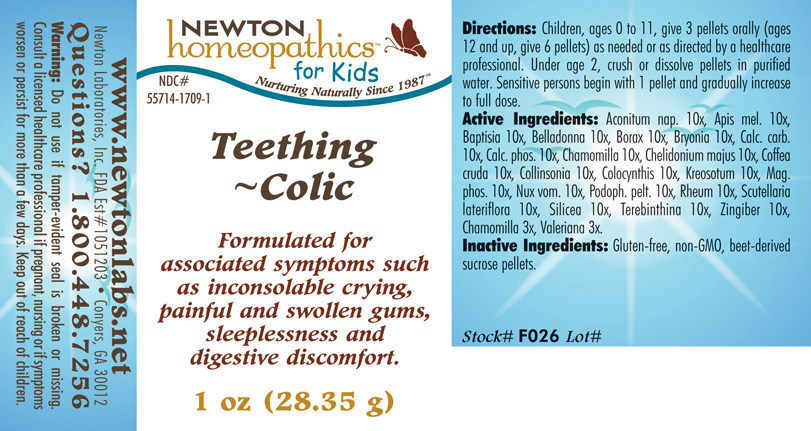 DRUG LABEL: Teething - Colic 
NDC: 55714-1709 | Form: PELLET
Manufacturer: Newton Laboratories, Inc.
Category: homeopathic | Type: HUMAN OTC DRUG LABEL
Date: 20110301

ACTIVE INGREDIENTS: Aconitum Napellus 10 [hp_X]/1 g; Apis Mellifera 10 [hp_X]/1 g; Baptisia Tinctoria 10 [hp_X]/1 g; Atropa Belladonna 10 [hp_X]/1 g; Sodium Borate 10 [hp_X]/1 g; Bryonia Alba Root 10 [hp_X]/1 g; Oyster Shell Calcium Carbonate, Crude 10 [hp_X]/1 g; Tribasic Calcium Phosphate 10 [hp_X]/1 g; Matricaria Recutita 10 [hp_X]/1 g; Chelidonium Majus 10 [hp_X]/1 g; Arabica Coffee Bean 10 [hp_X]/1 g; Collinsonia Canadensis Root 10 [hp_X]/1 g; Citrullus Colocynthis Fruit Pulp 10 [hp_X]/1 g; Wood Creosote 10 [hp_X]/1 g; Magnesium Phosphate, Dibasic Trihydrate 10 [hp_X]/1 g; Strychnos Nux-vomica Seed 10 [hp_X]/1 g; Podophyllum 10 [hp_X]/1 g; Rheum Officinale Root 10 [hp_X]/1 g; Scutellaria Lateriflora 10 [hp_X]/1 g; Silicon Dioxide 10 [hp_X]/1 g; Turpentine Oil 10 [hp_X]/1 g; Ginger 10 [hp_X]/1 g; Valerian 3 [hp_X]/1 g
INACTIVE INGREDIENTS: Sucrose

Teething - Colic

INDICATIONS & USAGE SECTION

Teething - Colic Formulated for associated symptoms such as inconsolable crying, painful and swollen gums, sleeplessness and digestive discomfort.

DOSAGE & ADMINISTRATION SECTION

Directions: Children, ages 0 to 11, give 3 pellets orally (ages 12 and up, give 6 pellets) as needed or as directed by a healthcare professional. Under age 2, crush or dissolve pellets in purified water. Sensitive persons begin with 1 pellet and gradually increase to full dose.

OTC - ACTIVE INGREDIENT SECTION

Aconitum nap. 10x, Apis mel. 10x, Baptisia 10x, Belladonna 10x, Borax 10x, Bryonia 10x, Calc. carb.10x, Calc. phos. 10x, Chamomilla 10x, Chelidonium majus 10x, Coffea cruda 10x, Collinsonia 10x, Colocynthis 10x, Kreosotum 10x, Mag.phos. 10x, Nux vom. 10x, Podoph. pelt. 10x, Rheum 10x, Scutellaria lateriflora 10x, Silicea 10x, Terebinthina 10x, Zingiber 10x, Chamomilla 3x, Valeriana 3x.

OTC - PURPOSE SECTION

Formulated for associated symptoms such as inconsolable crying, painful and swollen gums, sleeplessness and digestive discomfort.

INACTIVE INGREDIENT SECTION

Inactive Ingredients: Gluten-free, non-GMO, beet-derived sucrose pellets.

QUESTIONS SECTION

www.newtonlabs.net Newton Laboratories, Inc. FDA Est # 1051203 - Conyers, GA 30012
Questions? 1.800.448.7256

WARNINGS SECTION

Warning: Do not use if tamper - evident seal is broken or missing. Consult a licensed healthcare professional if pregnant, nursing or if symptoms worsen or persist for more than a few days. Keep out of reach of children.

OTC - PREGNANCY OR BREAST FEEDING SECTION

Consult a licensed healthcare professional if pregnant, nursing or if symptoms worsen or persist for more than a few days.

OTC - KEEP OUT OF REACH OF CHILDREN SECTION

Keep out of reach of children.